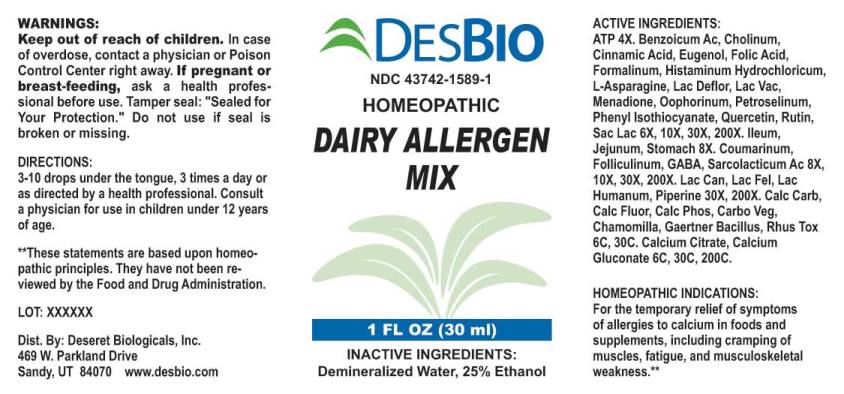 DRUG LABEL: Dairy Allergen Mix
NDC: 43742-1589 | Form: LIQUID
Manufacturer: Deseret Biologicals, Inc.
Category: homeopathic | Type: HUMAN OTC DRUG LABEL
Date: 20240911

ACTIVE INGREDIENTS: ADENOSINE TRIPHOSPHATE DISODIUM 4 [hp_X]/1 mL; BENZOIC ACID 6 [hp_X]/1 mL; CHOLINE HYDROXIDE 6 [hp_X]/1 mL; CINNAMIC ACID 6 [hp_X]/1 mL; EUGENOL 6 [hp_X]/1 mL; FOLIC ACID 6 [hp_X]/1 mL; FORMALDEHYDE 6 [hp_X]/1 mL; HISTAMINE DIHYDROCHLORIDE 6 [hp_X]/1 mL; ASPARAGINE MONOHYDRATE 6 [hp_X]/1 mL; SKIM MILK 6 [hp_X]/1 mL; COW MILK 6 [hp_X]/1 mL; MENADIONE 6 [hp_X]/1 mL; SUS SCROFA OVARY 6 [hp_X]/1 mL; PETROSELINUM CRISPUM 6 [hp_X]/1 mL; PHENYL ISOTHIOCYANATE 6 [hp_X]/1 mL; QUERCETIN 6 [hp_X]/1 mL; RUTIN 6 [hp_X]/1 mL; LACTOSE, UNSPECIFIED FORM 6 [hp_X]/1 mL; SUS SCROFA ILEUM 8 [hp_X]/1 mL; SUS SCROFA JEJUNUM 8 [hp_X]/1 mL; SUS SCROFA STOMACH 8 [hp_X]/1 mL; COUMARIN 8 [hp_X]/1 mL; ESTRONE 8 [hp_X]/1 mL; .GAMMA.-AMINOBUTYRIC ACID 8 [hp_X]/1 mL; LACTIC ACID, L- 8 [hp_X]/1 mL; CANIS LUPUS FAMILIARIS MILK 30 [hp_X]/1 mL; FELIS CATUS MILK 30 [hp_X]/1 mL; HUMAN MILK 30 [hp_X]/1 mL; PIPERINE 30 [hp_X]/1 mL; OYSTER SHELL CALCIUM CARBONATE, CRUDE 6 [hp_C]/1 mL; CALCIUM FLUORIDE 6 [hp_C]/1 mL; TRIBASIC CALCIUM PHOSPHATE 6 [hp_C]/1 mL; ACTIVATED CHARCOAL 6 [hp_C]/1 mL; MATRICARIA RECUTITA 6 [hp_C]/1 mL; SALMONELLA ENTERICA SUBSP. ENTERICA SEROVAR ENTERITIDIS 6 [hp_C]/1 mL; TOXICODENDRON PUBESCENS LEAF 6 [hp_C]/1 mL; CALCIUM CITRATE 6 [hp_C]/1 mL; CALCIUM GLUCONATE 6 [hp_C]/1 mL
INACTIVE INGREDIENTS: WATER; ALCOHOL

Drug Facts:

ACTIVE INGREDIENTS:

Adenosinum Triphosphoricum Dinatrum 4X, Benzoicum Acidum 6X, 10X, 30X, 200X, Cholinum 6X, 10X, 30X, 200X, Cinnamic Acid 6X, 10X, 30X, 200X, Eugenol 6X, 10X, 30X, 200X, Folic Acid 6X, 10X, 30X, 200X, Formalinum 6X, 10X, 30X, 200X, Histaminum Hydrochloricum 6X, 10X, 30X, 200X, L-Asparagine (Monohydrate) 6X, 10X, 30X, 200X, Lac Defloratum 6X, 10X, 30X, 200X, Lac Vaccinum 6X, 10X, 30X, 200X, Menadione 6X, 10X, 30X, 200X, Oophorinum (Suis) 6X, 10X, 30X, 200X, Petroselinum sativum 6X, 10X, 30X, 200X, Phenyl Isothiocyanate 6X, 10X, 30X, 200X, Quercetin 6X, 10X, 30X, 200X, Rutin 6X, 10X, 30X, 200X, Saccharum Lactis 6X, 10X, 30X, 200X, Ileum (Suis) 8X, Jejunum (Suis) 8X, Stomach (Suis) 8X, Coumarinum 6X, 10X, 30X, 200X, Folliculinum 6X, 10X, 30X, 200X, GABA (Gamma-Aminobutyric Acid) 6X, 10X, 30X, 200X, Sarcolacticum Acidum 8X, 10X, 30X, 200X, Lac Caninum 30X, 200X, Lac Felinum 30X, 200X, Lac Humanum 30X, 200X, Piperine 30X, 200X, Calcarea Carbonica 6C, 30C, Calcarea Fluorica 6C, 30C, Calcarea Phosphorica 6C, 30C, Carbo Vegetabilis 6C, 30C, Chamomilla 6C, 30C, Gaertner Bacillus (Bach) 6C, 30C, Rhus Tox 6C, 30C, Calcium Citrate 6C, 30C, 200C, Calcium Gluconate 6C, 30C, 200C.

HOMEOPATHIC INDICATIONS:

For the temporary relief of symptoms of allergies to calcium in foods and supplements, including cramping of muscles, fatigue, and musculoskeletal weakness.**

**These statements are based upon homeopathic principles. They have not been reviewed by the Food and Drug Administration.

WARNINGS:

Keep out of reach of children. In case of overdose, contact a physician or Poison Control Center right away.

If pregnant or breast-feeding, ask a health professional before use.

Tamper seal: "Sealed for Your Protection." Do not use if seal is broken or missing.

Keep out of reach of children. In case of overdose, get medical help or contact a Poison Control Center right away.

DIRECTIONS:

3-10 drops under the tongue, 3 times a day or as directed by a health professional. Consult a physician for use in children under 12 years of age.

HOMEOPATHIC INDICATIONS:

For the temporary relief of symptoms of allergies to calcium in foods and supplements, including cramping of muscles, fatigue, and musculoskeletal weakness.**

**These statements are based upon homeopathic principles. They have not been reviewed by the Food and Drug Administration.

INACTIVE INGREDIENTS:

Demineralized Water, 25% Ethanol

QUESTIONS:

Dist. By: Deseret Biologicals, Inc.

469 W. Parkland Drive

Sandy, UT 84070 www.desbio.com

PACKAGE LABEL DISPLAY:

DESBIO

NDC 43742-1589-1

HOMEOPATHIC

DAIRY ALLERGEN

MIX

1 FL OZ (30 ml)